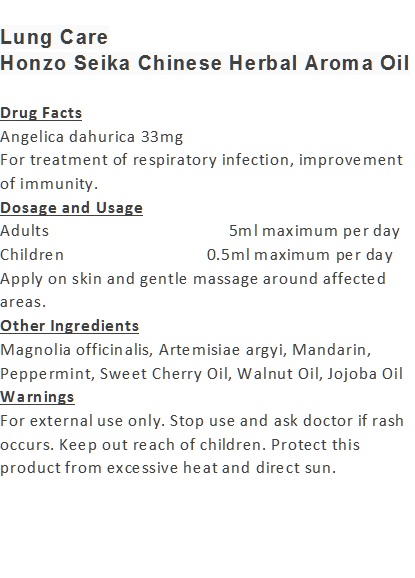 DRUG LABEL: Lung Care
NDC: 70470-9902 | Form: OIL
Manufacturer: Phytopia Co., Ltd.
Category: otc | Type: HUMAN OTC DRUG LABEL
Date: 20170101

ACTIVE INGREDIENTS: ANGELICA DAHURICA ROOT 33 mg/100 mL
INACTIVE INGREDIENTS: PEPPERMINT OIL; MANDARIN OIL; SWEET CHERRY SEED OIL; WALNUT OIL; JOJOBA OIL; MAGNOLIA OFFICINALIS FLOWER

Drug Facts

Angelica dahurica 33mg

Use

For treatment of respiratory infection, improvement of immunity.

Dosage Suggestion

Adults 5ml maximum per day

Children 0.5ml maximum per day

INACTIVE INGREDIENT

Other Ingredients

Magnolia officinalis, Artemisiae argyi, Mandarin, Peppermint, Sweet Cherry Oil, Walnut Oil, Jojoba Oil

Directions

Apply on skin and gentle massage around affected area.

Warnings

For external use only. Stop use and ask doctor if rash occurs. Keep out reach of children.

Other Information

Protect this product from excessive heat

and direct sun.

Warnings

For external use only. Stop use and ask doctor if rash occurs. Keep out reach of children.